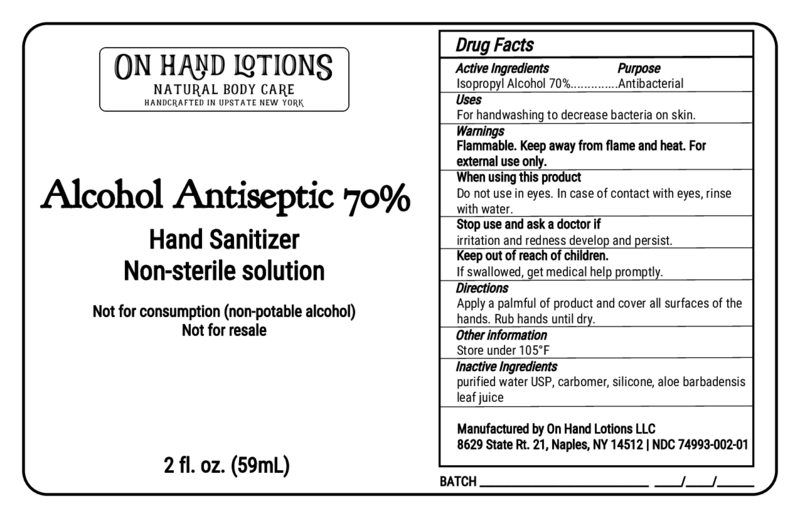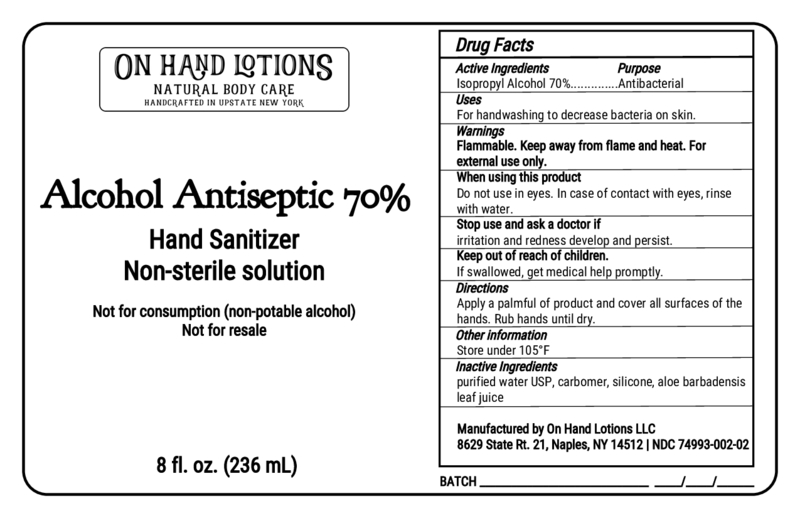 DRUG LABEL: Hand Sanitizer 70%
NDC: 74993-002 | Form: GEL
Manufacturer: On Hand Lotions, LLC
Category: otc | Type: HUMAN OTC DRUG LABEL
Date: 20200411

ACTIVE INGREDIENTS: ISOPROPYL ALCOHOL 70 mL/100 mL
INACTIVE INGREDIENTS: ALOE VERA LEAF 0.5 mL/100 mL; CARBOMER 980 0.24 mL/100 mL; WATER; POLYSILICONE-15 0.3 mL/100 mL

Hand Sanitizer 70%

The hand sanitizer is manufactured using only the following United States Pharmacopoeia (USP) grade ingredients in the preparation of the product (percentage in final product formulation):

1. Isopropyl Alcohol (70%, v/v) in an aqueous solution denatured according to Alcohol and Tobacco Tax and Trade Bureau regulations in 27 CFR part 20.
2. Carbomer.
3. Silicone.
4. Aloe.
5. Purified water USP.

The firm does not add other active or inactive ingredients. Different or additional ingredients may impact the quality and potency of the product.

Active Ingredient(s)

Isopropyl Alcohol 70% v/v. Purpose: Antiseptic

Purpose

Antiseptic, Hand Sanitizer

Use

Hand Sanitizer to help reduce bacteria that potentially can cause disease. For use when soap and water are not available.

Warnings

For external use only. Flammable. Keep away from heat or flame

Do not use

- in children less than 2 months of age
- on open skin wounds

When using this product keep out of eyes, ears, and mouth. In case of contact with eyes, rinse eyes thoroughly with water.
Stop use and ask a doctor if irritation or rash occurs. These may be signs of a serious condition.
Keep out of reach of children. If swallowed, get medical help or contact a Poison Control Center right away.

Stop use and ask a doctor if irritation or rash occurs. These may be signs of a serious condition.

Keep out of reach of children. If swallowed, get medical help or contact a Poison Control Center right away.

Directions

- Place enough product on hands to cover all surfaces. Rub hands together until dry.
- Supervise children under 6 years of age when using this product to avoid swallowing.

Other information

- Store between 15-30C (59-86F)
- Avoid freezing and excessive heat above 40C (104F)

Inactive ingredients

purified water USP, carbomer, silicone, aloe barbadensis leaf juice

Package Label - Principal Display Panel

59 ml NDC: 74993-002-01

236 ml NDC: 74993-002-02